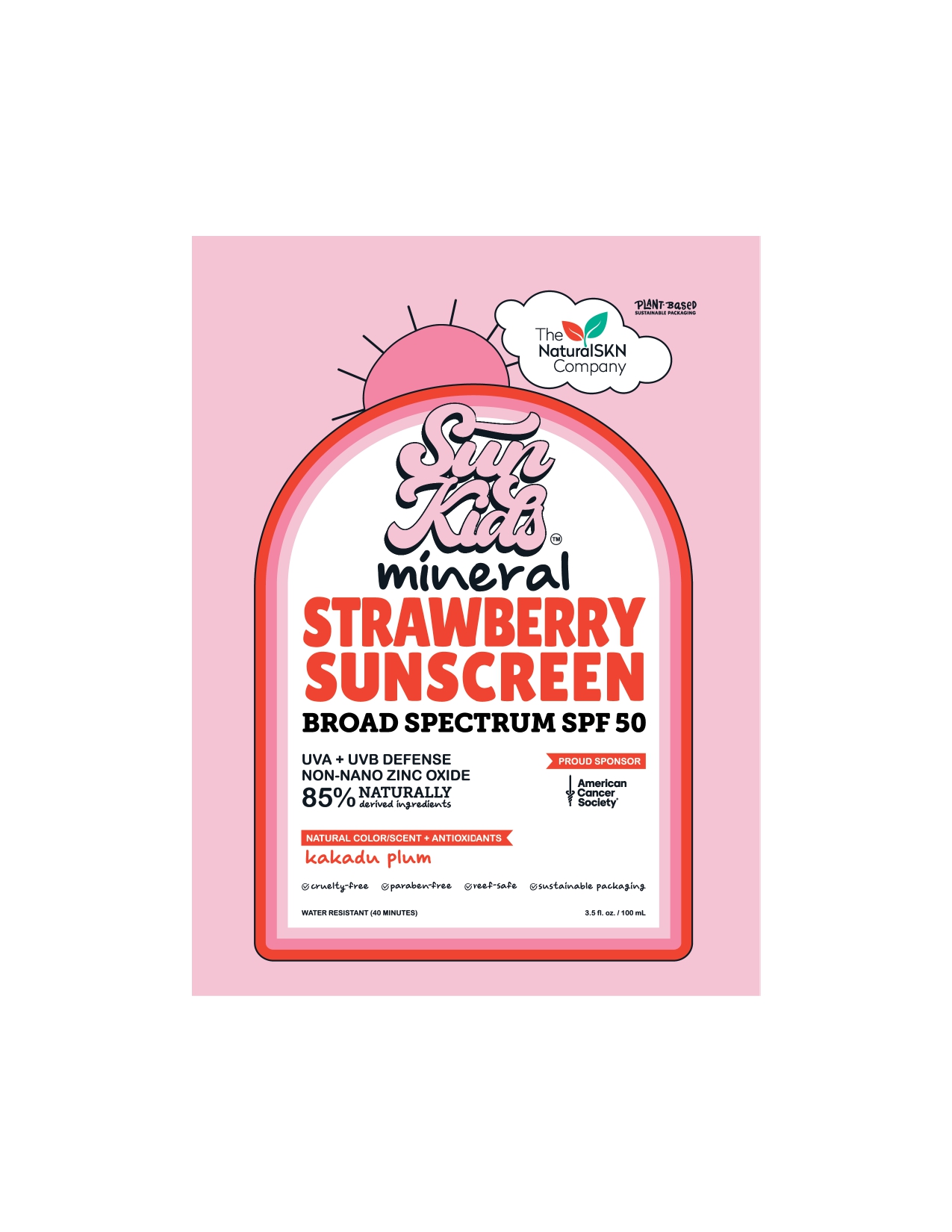 DRUG LABEL: Sun Kids mineral STRAWBERRY SUNSCREEN BROAD SPECTRUM SPF 50
NDC: 87138-001 | Form: CREAM
Manufacturer: The Natural SKN Company
Category: otc | Type: HUMAN OTC DRUG LABEL
Date: 20250930

ACTIVE INGREDIENTS: ZINC OXIDE 241 mg/1 mL
INACTIVE INGREDIENTS: DILINOLEIC ACID/BUTANEDIOL COPOLYMER; C12-15 ALKYL BENZOATE; GLYCERIN; C13-15 ALKANE; TRIHEPTANOIN; POLYGLYCERYL-10 DIOLEATE; POLYGLYCERYL-6 POLYRICINOLEATE; CAPRYLHYDROXAMIC ACID; FRAGARIA ANANASSA (STRAWBERRY) FRUIT JUICE; POLYHYDROXYSTEARIC ACID (2300 MW); CASTOR OIL/IPDI COPOLYMER; GLYCERYL CAPRYLATE; SODIUM CHLORIDE; DISTEARDIMONIUM HECTORITE; ISODODECANE; COCO-CAPRYLATE/CAPRATE; MELIA AZADIRACHTA LEAF; WATER; SQUALANE; PROPYLENE CARBONATE; CAPRYLIC/CAPRIC TRIGLYCERIDE; MORINGA OLEIFERA SEED OIL; LAUROYL LYSINE; COCONUT ALKANES

ACTIVE INGREDIENT

Zinc Oxide 24.1%

Warnings
For external use only
Do not use on damaged or broken skin.
When using this product keep out of eyes. Rinse with water to remove.
Stop use and ask a doctor if rash occurs
Keep out of reach of children. If swallowed, get medical help or contact a
Poison Control Center right away.

Uses

. helps prevent sunburn . if used as directed with other sun protection measures
(see Directions), decreases the risk of skin cancer and early skin aging caused by the sun

Do not use on damaged or broken skin.

Directions

. apply liberally and evenly 15 minutes before sun exposure
reapply:
. after 40 minutes of swimming or sweating
. at least every 2 hours
. children under 6 months of age: Ask a doctor
. Sun Protection Measures. Spending time in the sun increases your risk of skin cancer
and early skin aging. To decrease this risk, regularly use a sunscreen with a Broad
Spectrum SPF value of 15 or higher and other sun protection measures including:
. limit time in the sun, especially from 10 a.m .- 2 p.m.
· wear long-sleeved shirts, pants, hats, and sunglasses

Inactive ingredients

Water, C12-15 Alkyl Benzoate, Glycerin,Caprylic/CapricTriglyceride,
Polyglyceryl-6 Polyricinoleate,Coconut Alkanes,C13-15Alkane,Isododecane,Silica,Triheptanoin,
Polyhydroxystearic Acid,Coco-Caprylate/Caprate,Polyglyceryl-10 Dioleate,Melia Azadirachta
Extract, Glyceryl Caprylate, Fragrance, Sodium Chloride, Squalane, Hydrogenated
Phosphatidylcholine, Disteardimonium Hectorite, Saccharomyces Ferment, Propylene
Carbonate, Dilinoleic Acid/Butanediol Copolymer, Caprylhydroxamic Acid, Tocopheryl
Acetate, Moringa Oleifera Seed Oil, Lauroyl Lysine, Terminalia Ferdinandiana Fruit Extract,
Castor Oil/IPDI Copolymer, Fragaria Ananassa (Strawberry) Fruit Extract.

Other information

. protect product from excessive heat and direct sun

Keep out of reach of children. If swallowed, get medical help or contact a Poison Control Center right away